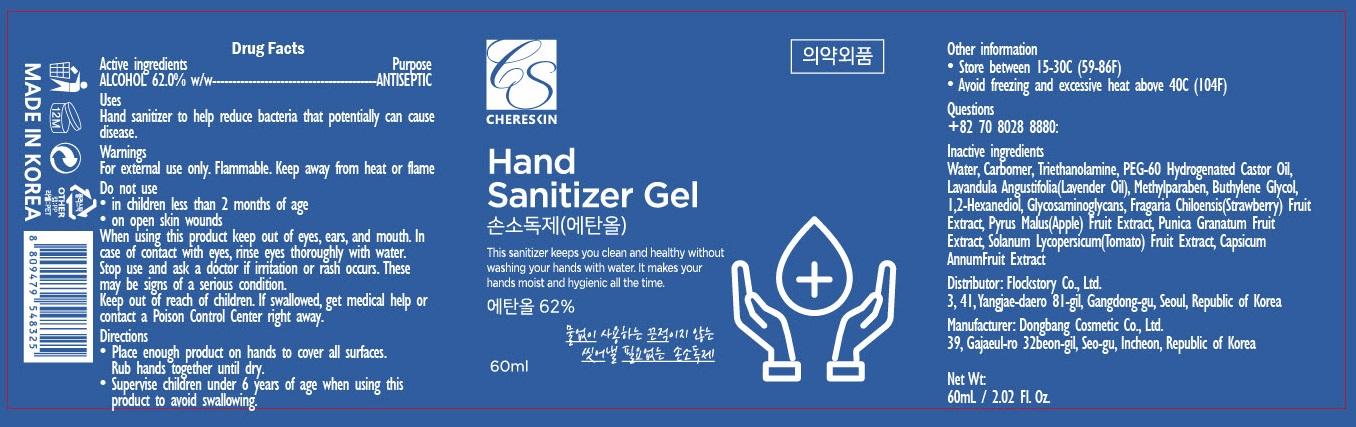 DRUG LABEL: Chereskin Hand Sanitizer
NDC: 74779-010 | Form: GEL
Manufacturer: Flockstory Co., Ltd.
Category: otc | Type: HUMAN OTC DRUG LABEL
Date: 20200418

ACTIVE INGREDIENTS: ALCOHOL 37.2 g/60 mL
INACTIVE INGREDIENTS: Water; CARBOMER HOMOPOLYMER, UNSPECIFIED TYPE; TROLAMINE; PEG-60 Hydrogenated Castor Oil; lavender oil; Methylparaben; Butylene Glycol; 1,2-Hexanediol; BEACH STRAWBERRY; APPLE; POMEGRANATE; TOMATO; PAPRIKA

ACTIVE INGREDIENT

Active ingredients: ALCOHOL 62.0% w/w

INACTIVE INGREDIENT

Inactive Ingredients:

Water, Carbomer, Triethanolamine, PEG-60 Hydrogenated Castor Oil, Lavandula Angustifolia(Lavender Oil), Methylparaben, Buthylene Glycol, 1,2-Hexanediol, Glycosaminoglycans, Fragaria Chiloensis(Strawberry) Fruit Extract, Pyrus Malus(Apple) Fruit Extract, Punica Granatum Fruit Extract, Solanum Lycopersicum (Tomato) Fruit Extract, Capsicum AnnumFruit Extract

PURPOSE

Purpose: ANTISEPTIC

WARNINGS

For external use only. Flammable. Keep away from heat or flame
--------------------------------------------------------------------------------------------------------
Do not use
• in children less than 2 months of age
• on open skin wounds
--------------------------------------------------------------------------------------------------------
When using this product keep out of eyes, ears, and mouth. In case of contact with eyes, rinse eyes thoroughly with water.
--------------------------------------------------------------------------------------------------------
Stop use and ask a doctor if irritation or rash occurs. These may be signs of a serious condition.

Keep out of reach of children. If swallowed, get medical help or contact a Poison Control Center right away.

Uses

■ Hand sanitizer to help reduce bacteria that potentially can cause disease.

Directions

• Place enough product on hands to cover all surfaces. Rub hands together until dry.
• Supervise children under 6 years of age when using this product to avoid swallowing.

Other Information

• Store between 15-30C (59-86F)
• Avoid freezing and excessive heat above 40C (104F)

QUESTIONS

+82 70 8028 8880